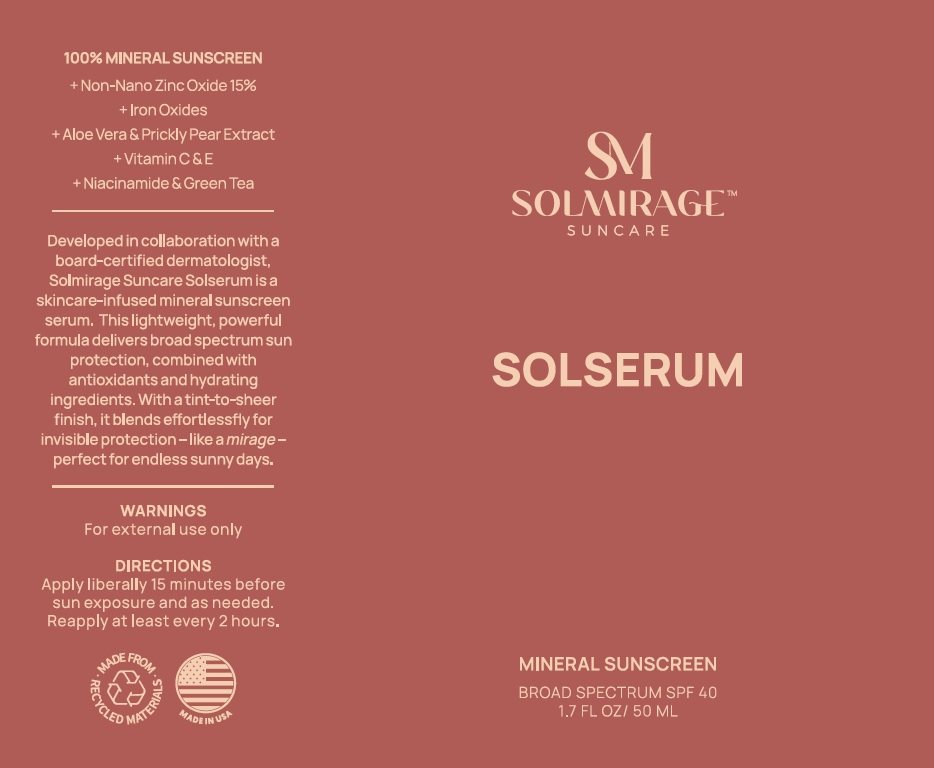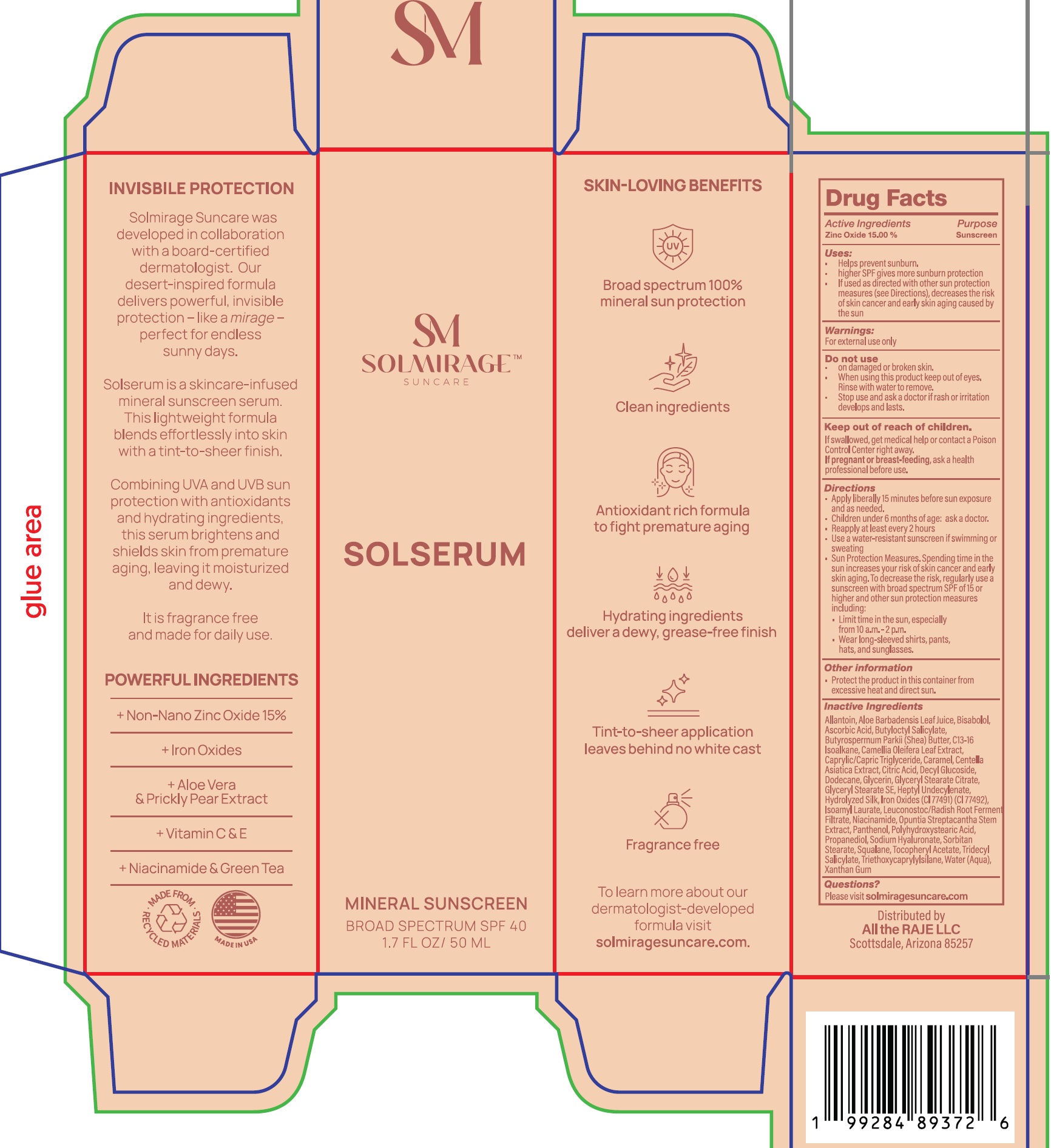 DRUG LABEL: SM SOLMIRAGE SUNCARE Solserum Mineral Sunscreen SPF 40
NDC: 87018-875 | Form: LIQUID
Manufacturer: ALL THE RAJE, LLC
Category: otc | Type: HUMAN OTC DRUG LABEL
Date: 20250813

ACTIVE INGREDIENTS: ZINC OXIDE 150 mg/1 mL
INACTIVE INGREDIENTS: DODECANE; GLYCERIN; GLYCERYL STEARATE CITRATE; GLYCERYL STEARATE SE; HEPTYL UNDECYLENATE; FERRIC OXIDE RED; FERRIC OXIDE YELLOW; ISOAMYL LAURATE; LEUCONOSTOC/RADISH ROOT FERMENT FILTRATE; NIACINAMIDE; OPUNTIA STREPTACANTHA STEM; PANTHENOL; PROPANEDIOL; SODIUM HYALURONATE; SORBITAN STEARATE; SQUALANE; .ALPHA.-TOCOPHEROL ACETATE; TRIDECYL SALICYLATE; TRIETHOXYCAPRYLYLSILANE; WATER; XANTHAN GUM; ALLANTOIN; ALOE VERA LEAF; BISABOLOL; ASCORBIC ACID; BUTYLOCTYL SALICYLATE; SHEA BUTTER; C13-16 ISOPARAFFIN; CAMELLIA OLEIFERA LEAF; MEDIUM-CHAIN TRIGLYCERIDES; CARAMEL; CENTELLA ASIATICA TRITERPENOIDS; CITRIC ACID MONOHYDRATE; DECYL GLUCOSIDE

SM SOLMIRAGE SUNCARE Solserum Mineral Sunscreen SPF 40

Active Ingredients

Zinc Oxide 15.00%

Purpose

Sunscreen

Uses:

- Helps prevent sunburn.
- higher SPF gives more sunburn protection
- If used as directed with other sun protection measures (see Directions), decreases the risk of skin cancer and early skin aging caused by the sun

Warnings:

For external use only

Do not use

- on damaged or broken skin.

When using this product

- keep out of eyes. Rinse with water to remove.

Stop use and ask a doctor if

- rash or irritation develops and lasts.

Keep out of reach of children.

If swallowed, get medical help or contact a Poison Control Center right away.

If pregnant or breast-feeding,

ask a health professional before use.

Directions

- Apply liberally 15 minutes before sun exposure and as needed.
- Children under 6 months of age: ask a doctor.
- Reapply at least every 2 hours
- Use a water-resistant sunscreen if swimming or sweating
- Sun Protection Measures. Spending time in the sun increases your risk of skin cancer and early skin aging. To decrease the risk, regularly use a sunscreen with broad spectrum SPF of 15 or higher and other sun protection measures including:
- Limit time in the sun, especially from 10 a.m.-2 p.m.
- Wear long-sleeved shirts, pants, hats, and sunglasses.

Other information

- Protect the product in this container from excessive heat and direct sun.

Inactive ingredients

Allantoin, Aloe Barbadensis Leaf Juice, Bisabolol, Ascorbic Acid, Butyloctyl Salicylate, Butyrospermum Parkii (Shea) Butter, C13-16 Isoalkane, Camellia Oleifera Leaf Extract, Caprylic/Capric Triglyceride, Caramel, Centella Asiatica Extract, Citric Acid, Decyl Glucoside, Dodecane, Glycerin, Glyceryl Stearate Citrate, Glyceryl Stearate SE, Heptyl Undecylenate, Hydrolyzed Silk, Iron Oxides (CI 77491) (CI 77492), Isoamyl Laurate, Leconostoc/Radish Root Ferment Filtrate, Niacinamide, Opuntia Streptacantha Stem Extract, Panthenol, Polyhydroxystearic Acid, Propanediol, Sodium Hyaluronate, Sorbitan Stearate, Squalane, Tocopheryl Acetate, Tridecyl Salicylate, Triethoxycaprylylsilane, Water (Aqua), Xanthan Gum

Questions?

Please visit solmiragesuncare.com